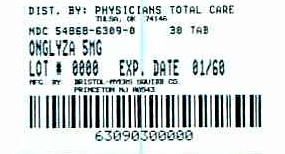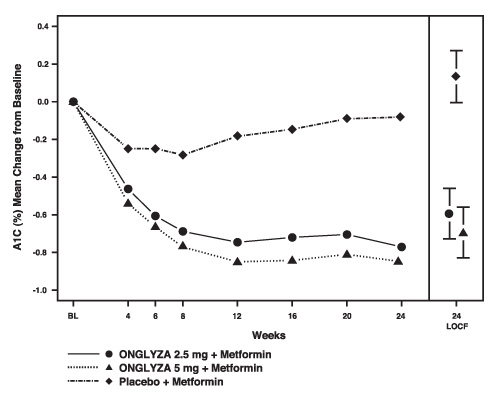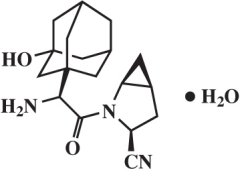 DRUG LABEL: ONGLYZA
NDC: 54868-6309 | Form: TABLET, FILM COATED
Manufacturer: Physicians Total Care, Inc.
Category: prescription | Type: HUMAN PRESCRIPTION DRUG LABEL
Date: 20120109

ACTIVE INGREDIENTS: saxagliptin hydrochloride 5 mg/1 1
INACTIVE INGREDIENTS: lactose monohydrate; cellulose, microcrystalline; croscarmellose sodium; magnesium stearate

HIGHLIGHTS OF PRESCRIBING INFORMATION

These highlights do not include all the information needed to use ONGLYZA safely and effectively. See full prescribing information for ONGLYZA.
ONGLYZA (saxagliptin) tablets
Initial U.S. Approval: 2009

RECENT MAJOR CHANGES

Indications and Usage
Important Limitations of Use (1.2) 11/2011
Dosage and Administration
Recommended Dosing (2.1) 12/2011
Concomitant Use with an Insulin Secretagogue (e.g., Sulfonylurea) or with Insulin (2.4) 12/2011
Contraindications (4) 11/2011
Warnings and Precautions
Pancreatitis (5.1) 11/2011
Use with Medications Known to Cause Hypoglycemia (5.2) 12/2011
Hypersensitivity Reactions (5.3) 11/2011

1 INDICATIONS AND USAGE

ONGLYZA is a dipeptidyl peptidase-4 (DPP4) inhibitor indicated as an adjunct to diet and exercise to improve glycemic control in adults with type 2 diabetes mellitus in multiple clinical settings. (1.1, 14)

Important limitations of use:

- Should not be used for the treatment of type 1 diabetes mellitus or diabetic ketoacidosis. (1.2)
- Has not been studied in patients with a history of pancreatitis. (1.2, 5.1)

2 DOSAGE AND ADMINISTRATION

- The recommended dose is 2.5 mg or 5 mg once daily taken regardless of meals. (2.1)
- 2.5 mg daily is recommended for patients with moderate or severe renal impairment, or end-stage renal disease (CrCl ≤50 mL/min). Assess renal function before starting ONGLYZA and periodically thereafter. (2.2)
- 2.5 mg daily is recommended for patients also taking strong cytochrome P450 3A4/5 (CYP3A4/5) inhibitors (e.g., ketoconazole). (2.3, 7.1)

3 DOSAGE FORMS AND STRENGTHS

- Tablets: 5 mg and 2.5 mg (3)

4 CONTRAINDICATIONS

- History of a serious hypersensitivity reaction (e.g., anaphylaxis, angioedema, exfoliative skin conditions) to ONGLYZA. (4)

5 WARNINGS AND PRECAUTIONS

- There have been postmarketing reports of acute pancreatitis. If pancreatitis is suspected, promptly discontinue ONGLYZA. (5.1)
- When used with an insulin secretagogue (e.g., sulfonylurea) or insulin, a lower dose of the insulin secretagogue or insulin may be required to minimize the risk of hypoglycemia. (5.2)
- There have been postmarketing reports of serious hypersensitivity reactions in patients treated with ONGLYZA such as anaphylaxis, angioedema, and exfoliative skin conditions. In such cases, promptly discontinue ONGLYZA, assess for other potential causes, institute appropriate monitoring and treatment, and initiate alternative treatment for diabetes. (5.3, 6.2)
- There have been no clinical studies establishing conclusive evidence of macrovascular risk reduction with ONGLYZA or any other antidiabetic drug. (5.4)

6 ADVERSE REACTIONS

- Adverse reactions reported in ≥5% of patients treated with ONGLYZA and more commonly than in patients treated with placebo are: upper respiratory tract infection, urinary tract infection, and headache. (6.1)
- Peripheral edema was reported more commonly in patients treated with the combination of ONGLYZA and a thiazolidinedione (TZD) than in patients treated with the combination of placebo and TZD. (6.1)
- In the add-on to sulfonylurea and add-on to insulin trials, confirmed hypoglycemia was reported more commonly in patients treated with ONGLYZA compared to placebo. (6.1)
- Hypersensitivity-related events (e.g., urticaria, facial edema) were reported more commonly in patients treated with ONGLYZA than in patients treated with placebo. (6.1)

To report SUSPECTED ADVERSE REACTIONS, contact Bristol-Myers Squibb at 1-800-721-5072 or FDA at 1-800-FDA-1088 or www.fda.gov/medwatch

7 DRUG INTERACTIONS

- Coadministration with strong CYP3A4/5 inhibitors (e.g., ketoconazole) significantly increases saxagliptin concentrations. Recommend limiting ONGLYZA dose to 2.5 mg once daily. (2.3, 7.1)

8 USE IN SPECIFIC POPULATIONS

- No adequate and well-controlled studies in pregnant women. (8.1)
- Safety and effectiveness of ONGLYZA in pediatric patients below the age of 18 have not been established. (8.4)

FULL PRESCRIBING INFORMATION

1 INDICATIONS AND USAGE

1.1 Monotherapy and Combination Therapy

ONGLYZA is indicated as an adjunct to diet and exercise to improve glycemic control in adults with type 2 diabetes mellitus in multiple clinical settings. [See Clinical Studies (14).]

1.2 Important Limitations of Use

ONGLYZA should not be used for the treatment of type 1 diabetes mellitus or diabetic ketoacidosis, as it would not be effective in these settings.

ONGLYZA has not been studied in patients with a history of pancreatitis. It is unknown whether patients with a history of pancreatitis are at an increased risk for the development of pancreatitis while using ONGLYZA. [See Warnings and Precautions (5.1).]

2 DOSAGE AND ADMINISTRATION

2.1 Recommended Dosing

The recommended dose of ONGLYZA is 2.5 mg or 5 mg once daily taken regardless of meals.

ONGLYZA tablets must not be split or cut.

2.2 Patients with Renal Impairment

No dosage adjustment for ONGLYZA is recommended for patients with mild renal impairment (creatinine clearance [CrCl] >50 mL/min).

The dose of ONGLYZA is 2.5 mg once daily for patients with moderate or severe renal impairment, or with end-stage renal disease (ESRD) requiring hemodialysis (creatinine clearance [CrCl] ≤50 mL/min) [see Clinical Pharmacology (12.3) and Clinical Studies (14.3)]. ONGLYZA should be administered following hemodialysis. ONGLYZA has not been studied in patients undergoing peritoneal dialysis.

Because the dose of ONGLYZA should be limited to 2.5 mg based upon renal function, assessment of renal function is recommended prior to initiation of ONGLYZA and periodically thereafter. Renal function can be estimated from serum creatinine using the Cockcroft-Gault formula or Modification of Diet in Renal Disease formula. [See Clinical Pharmacology (12.3).]

2.3 Strong CYP3A4/5 Inhibitors

The dose of ONGLYZA is 2.5 mg once daily when coadministered with strong cytochrome P450 3A4/5 (CYP3A4/5) inhibitors (e.g., ketoconazole, atazanavir, clarithromycin, indinavir, itraconazole, nefazodone, nelfinavir, ritonavir, saquinavir, and telithromycin). [See Drug Interactions (7.1) and Clinical Pharmacology (12.3).]

2.4 Concomitant Use with an Insulin Secretagogue (e.g., Sulfonylurea) or with Insulin

When ONGLYZA is used in combination with an insulin secretagogue (e.g., sulfonylurea) or with insulin, a lower dose of the insulin secretagogue or insulin may be required to minimize the risk of hypoglycemia. [See Warnings and Precautions (5.1).]

3 DOSAGE FORMS AND STRENGTHS

- ONGLYZA (saxagliptin) 5 mg tablets are pink, biconvex, round, film-coated tablets with “5” printed on one side and “4215” printed on the reverse side, in blue ink.

- ONGLYZA (saxagliptin) 2.5 mg tablets are pale yellow to light yellow, biconvex, round, film-coated tablets with “2.5” printed on one side and “4214” printed on the reverse side, in blue ink.

4 CONTRAINDICATIONS

History of a serious hypersensitivity reaction to ONGLYZA, such as anaphylaxis, angioedema, or exfoliative skin conditions. [See Warnings and Precautions (5.3) and Adverse Reactions (6.2).]

5 WARNINGS AND PRECAUTIONS

5.1 Pancreatitis

There have been postmarketing reports of acute pancreatitis in patients taking ONGLYZA. After initiation of ONGLYZA, patients should be observed carefully for signs and symptoms of pancreatitis. If pancreatitis is suspected, ONGLYZA should promptly be discontinued and appropriate management should be initiated. It is unknown whether patients with a history of pancreatitis are at increased risk for the development of pancreatitis while using ONGLYZA.

5.2 Use with Medications Known to Cause Hypoglycemia

When ONGLYZA was used in combination with a sulfonylurea or with insulin, medications known to cause hypoglycemia, the incidence of confirmed hypoglycemia was increased over that of placebo used in combination with a sulfonylurea or with insulin. [See Adverse Reactions (6.1).] Therefore, a lower dose of the insulin secretagogue or insulin may be required to minimize the risk of hypoglycemia when used in combination with ONGLYZA. [See Dosage and Administration (2.4).]

5.3 Hypersensitivity Reactions

There have been postmarketing reports of serious hypersensitivity reactions in patients treated with ONGLYZA. These reactions include anaphylaxis, angioedema, and exfoliative skin conditions. Onset of these reactions occurred within the first 3 months after initiation of treatment with ONGLYZA, with some reports occurring after the first dose. If a serious hypersensitivity reaction is suspected, discontinue ONGLYZA, assess for other potential causes for the event, and institute alternative treatment for diabetes. [See Adverse Reactions (6.2).]

Use caution in a patient with a history of angioedema to another dipeptidyl peptidase-4 (DPP4) inhibitor because it is unknown whether such patients will be predisposed to angioedema with ONGLYZA.

5.4 Macrovascular Outcomes

There have been no clinical studies establishing conclusive evidence of macrovascular risk reduction with ONGLYZA or any other antidiabetic drug.

6 ADVERSE REACTIONS

6.1 Clinical Trials Experience

Because clinical trials are conducted under widely varying conditions, adverse reaction rates observed in the clinical trials of a drug cannot be directly compared to rates in the clinical trials of another drug and may not reflect the rates observed in practice.

Monotherapy and Add-On Combination Therapy

In two placebo-controlled monotherapy trials of 24-weeks duration, patients were treated with ONGLYZA 2.5 mg daily, ONGLYZA 5 mg daily, and placebo. Three 24-week, placebo-controlled, add-on combination therapy trials were also conducted: one with metformin, one with a thiazolidinedione (pioglitazone or rosiglitazone), and one with glyburide. In these three trials, patients were randomized to add-on therapy with ONGLYZA 2.5 mg daily, ONGLYZA 5 mg daily, or placebo. A saxagliptin 10 mg treatment arm was included in one of the monotherapy trials and in the add-on combination trial with metformin.

In a prespecified pooled analysis of the 24-week data (regardless of glycemic rescue) from the two monotherapy trials, the add-on to metformin trial, the add-on to thiazolidinedione (TZD) trial, and the add-on to glyburide trial, the overall incidence of adverse events in patients treated with ONGLYZA 2.5 mg and ONGLYZA 5 mg was similar to placebo (72.0% and 72.2% versus 70.6%, respectively). Discontinuation of therapy due to adverse events occurred in 2.2%, 3.3%, and 1.8% of patients receiving ONGLYZA 2.5 mg, ONGLYZA 5 mg, and placebo, respectively. The most common adverse events (reported in at least 2 patients treated with ONGLYZA 2.5 mg or at least 2 patients treated with ONGLYZA 5 mg) associated with premature discontinuation of therapy included lymphopenia (0.1% and 0.5% versus 0%, respectively), rash (0.2% and 0.3% versus 0.3%), blood creatinine increased (0.3% and 0% versus 0%), and blood creatine phosphokinase increased (0.1% and 0.2% versus 0%). The adverse reactions in this pooled analysis reported (regardless of investigator assessment of causality) in ≥5% of patients treated with ONGLYZA 5 mg, and more commonly than in patients treated with placebo are shown in Table 1.

Table 1: Adverse Reactions (Regardless of Investigator Assessment of Causality) in Placebo-Controlled Trials* Reported in ≥5% of Patients Treated with ONGLYZA 5 mg and More Commonly than in Patients Treated with Placebo
 | Number (%) of Patients
 | ONGLYZA 5 mg N=882 | Placebo N=799
Upper respiratory tract infection | 68 (7.7) | 61 (7.6)
Urinary tract infection | 60 (6.8) | 49 (6.1)
Headache | 57 (6.5) | 47 (5.9)
* The 5 placebo-controlled trials include two monotherapy trials and one add-on combination therapy trial with each of the following: metformin, thiazolidinedione, or glyburide. Table shows 24-week data regardless of glycemic rescue.

In patients treated with ONGLYZA 2.5 mg, headache (6.5%) was the only adverse reaction reported at a rate ≥5% and more commonly than in patients treated with placebo.

In this pooled analysis, adverse reactions that were reported in ≥2% of patients treated with ONGLYZA 2.5 mg or ONGLYZA 5 mg and ≥1% more frequently compared to placebo included: sinusitis (2.9% and 2.6% versus 1.6%, respectively), abdominal pain (2.4% and 1.7% versus 0.5%), gastroenteritis (1.9% and 2.3% versus 0.9%), and vomiting (2.2% and 2.3% versus 1.3%).

In the add-on to TZD trial, the incidence of peripheral edema was higher for ONGLYZA 5 mg versus placebo (8.1% and 4.3%, respectively). The incidence of peripheral edema for ONGLYZA 2.5 mg was 3.1%. None of the reported adverse reactions of peripheral edema resulted in study drug discontinuation. Rates of peripheral edema for ONGLYZA 2.5 mg and ONGLYZA 5 mg versus placebo were 3.6% and 2% versus 3% given as monotherapy, 2.1% and 2.1% versus 2.2% given as add-on therapy to metformin, and 2.4% and 1.2% versus 2.2% given as add-on therapy to glyburide.

The incidence rate of fractures was 1.0 and 0.6 per 100 patient-years, respectively, for ONGLYZA (pooled analysis of 2.5 mg, 5 mg, and 10 mg) and placebo. The incidence rate of fracture events in patients who received ONGLYZA did not increase over time. Causality has not been established and nonclinical studies have not demonstrated adverse effects of saxagliptin on bone.

An event of thrombocytopenia, consistent with a diagnosis of idiopathic thrombocytopenic purpura, was observed in the clinical program. The relationship of this event to ONGLYZA is not known.

Use in Renal Impairment

ONGLYZA 2.5 mg was compared to placebo in a 12-week trial in 170 patients with type 2 diabetes and moderate or severe renal impairment or end-stage renal disease (ESRD). The incidence of adverse events, including serious adverse events and discontinuations due to adverse events, was similar between ONGLYZA and placebo.

Use in Combination with Insulin

In the add-on to insulin trial [see Clinical Studies (14.2)], the incidence of adverse events, including serious adverse events and discontinuations due to adverse events, was similar between ONGLYZA and placebo, except for confirmed hypoglycemia (see Hypoglycemia subsection).

Adverse Reactions Associated with ONGLYZA Coadministered with Metformin in Treatment-Naive Patients with Type 2 Diabetes

Table 2 shows the adverse reactions reported (regardless of investigator assessment of causality) in ≥5% of patients participating in an additional 24-week, active-controlled trial of coadministered ONGLYZA and metformin in treatment-naive patients.

Table 2: Initial Therapy with Combination of ONGLYZA and Metformin in Treatment-Naive Patients: Adverse Reactions Reported (Regardless of Investigator Assessment of Causality) in ≥5% of Patients Treated with Combination Therapy of ONGLYZA 5 mg Plus Metformin (and More Commonly than in Patients Treated with Metformin Alone)
 | Number (%) of Patients
 | ONGLYZA 5 mg + Metformin* N=320 | Metformin* N=328
Headache | 24 (7.5) | 17 (5.2)
Nasopharyngitis | 22 (6.9) | 13 (4.0)
* Metformin was initiated at a starting dose of 500 mg daily and titrated up to a maximum of 2000 mg daily.

Hypoglycemia

Adverse reactions of hypoglycemia were based on all reports of hypoglycemia. A concurrent glucose measurement was not required or was normal in some patients. Therefore, it is not possible to conclusively determine that all these reports reflect true hypoglycemia.

In the add-on to glyburide study, the overall incidence of reported hypoglycemia was higher for ONGLYZA 2.5 mg and ONGLYZA 5 mg (13.3% and 14.6%) versus placebo (10.1%). The incidence of confirmed hypoglycemia in this study, defined as symptoms of hypoglycemia accompanied by a fingerstick glucose value of ≤50 mg/dL, was 2.4% and 0.8% for ONGLYZA 2.5 mg and ONGLYZA 5 mg and 0.7% for placebo [see Warnings and Precautions (5.2)]. The incidence of reported hypoglycemia for ONGLYZA 2.5 mg and ONGLYZA 5 mg versus placebo given as monotherapy was 4.0% and 5.6% versus 4.1%, respectively, 7.8% and 5.8% versus 5% given as add-on therapy to metformin, and 4.1% and 2.7% versus 3.8% given as add-on therapy to TZD. The incidence of reported hypoglycemia was 3.4% in treatment-naive patients given ONGLYZA 5 mg plus metformin and 4.0% in patients given metformin alone.

In the active-controlled trial comparing add-on therapy with ONGLYZA 5 mg to glipizide in patients inadequately controlled on metformin alone, the incidence of reported hypoglycemia was 3% (19 events in 13 patients) with ONGLYZA 5 mg versus 36.3% (750 events in 156 patients) with glipizide. Confirmed symptomatic hypoglycemia (accompanying fingerstick blood glucose ≤50 mg/dL) was reported in none of the ONGLYZA-treated patients and in 35 glipizide-treated patients (8.1%) (p<0.0001).

During 12 weeks of treatment in patients with moderate or severe renal impairment or ESRD, the overall incidence of reported hypoglycemia was 20% among patients treated with ONGLYZA 2.5 mg and 22% among patients treated with placebo. Four ONGLYZA-treated patients (4.7%) and three placebo-treated patients (3.5%) reported at least one episode of confirmed symptomatic hypoglycemia (accompanying fingerstick glucose ≤50 mg/dL).

In the add-on to insulin trial, the overall incidence of reported hypoglycemia was 18.4% for ONGLYZA 5 mg and 19.9% for placebo. However, the incidence of confirmed symptomatic hypoglycemia (accompanying fingerstick blood glucose ≤50 mg/dL) was higher with ONGLYZA 5 mg (5.3%) versus placebo (3.3%) [see Warnings and Precautions (5.2)].

Hypersensitivity Reactions

Hypersensitivity-related events, such as urticaria and facial edema in the 5-study pooled analysis up to Week 24 were reported in 1.5%, 1.5%, and 0.4% of patients who received ONGLYZA 2.5 mg, ONGLYZA 5 mg, and placebo, respectively. None of these events in patients who received ONGLYZA required hospitalization or were reported as life-threatening by the investigators. One saxagliptin-treated patient in this pooled analysis discontinued due to generalized urticaria and facial edema.

Infections

In the unblinded, controlled, clinical trial database for saxagliptin to date, there have been 6 (0.12%) reports of tuberculosis among the 4959 saxagliptin-treated patients (1.1 per 1000 patient-years) compared to no reports of tuberculosis among the 2868 comparator-treated patients. Two of these six cases were confirmed with laboratory testing. The remaining cases had limited information or had presumptive diagnoses of tuberculosis. None of the six cases occurred in the United States or in Western Europe. One case occurred in Canada in a patient originally from Indonesia who had recently visited Indonesia. The duration of treatment with saxagliptin until report of tuberculosis ranged from 144 to 929 days. Post-treatment lymphocyte counts were consistently within the reference range for four cases. One patient had lymphopenia prior to initiation of saxagliptin that remained stable throughout saxagliptin treatment. The final patient had an isolated lymphocyte count below normal approximately four months prior to the report of tuberculosis. There have been no spontaneous reports of tuberculosis associated with saxagliptin use. Causality has not been estimated and there are too few cases to date to determine whether tuberculosis is related to saxagliptin use.

There has been one case of a potential opportunistic infection in the unblinded, controlled clinical trial database to date in a saxagliptin-treated patient who developed suspected foodborne fatal salmonella sepsis after approximately 600 days of saxagliptin therapy. There have been no spontaneous reports of opportunistic infections associated with saxagliptin use.

Vital Signs

No clinically meaningful changes in vital signs have been observed in patients treated with ONGLYZA.

Laboratory Tests

Absolute Lymphocyte Counts

There was a dose-related mean decrease in absolute lymphocyte count observed with ONGLYZA. From a baseline mean absolute lymphocyte count of approximately 2200 cells/microL, mean decreases of approximately 100 and 120 cells/microL with ONGLYZA 5 mg and 10 mg, respectively, relative to placebo were observed at 24 weeks in a pooled analysis of five placebo-controlled clinical studies. Similar effects were observed when ONGLYZA 5 mg was given in initial combination with metformin compared to metformin alone. There was no difference observed for ONGLYZA 2.5 mg relative to placebo. The proportion of patients who were reported to have a lymphocyte count ≤750 cells/microL was 0.5%, 1.5%, 1.4%, and 0.4% in the saxagliptin 2.5 mg, 5 mg, 10 mg, and placebo groups, respectively. In most patients, recurrence was not observed with repeated exposure to ONGLYZA although some patients had recurrent decreases upon rechallenge that led to discontinuation of ONGLYZA. The decreases in lymphocyte count were not associated with clinically relevant adverse reactions.

The clinical significance of this decrease in lymphocyte count relative to placebo is not known. When clinically indicated, such as in settings of unusual or prolonged infection, lymphocyte count should be measured. The effect of ONGLYZA on lymphocyte counts in patients with lymphocyte abnormalities (e.g., human immunodeficiency virus) is unknown.

Platelets

ONGLYZA did not demonstrate a clinically meaningful or consistent effect on platelet count in the six, double-blind, controlled clinical safety and efficacy trials.

6.2 Postmarketing Experience

Additional adverse reactions have been identified during postapproval use of ONGLYZA. Because these reactions are reported voluntarily from a population of uncertain size, it is generally not possible to reliably estimate their frequency or establish a causal relationship to drug exposure.

- Hypersensitivity reactions including anaphylaxis, angioedema, and exfoliative skin conditions. [See Contraindications (4) and Warnings and Precautions (5.3).]
- Acute pancreatitis. [See Indications and Usage (1.2) and Warnings and Precautions (5.1).]

7 DRUG INTERACTIONS

7.1 Strong Inhibitors of CYP3A4/5 Enzymes

Ketoconazole significantly increased saxagliptin exposure. Similar significant increases in plasma concentrations of saxagliptin are anticipated with other strong CYP3A4/5 inhibitors (e.g., atazanavir, clarithromycin, indinavir, itraconazole, nefazodone, nelfinavir, ritonavir, saquinavir, and telithromycin). The dose of ONGLYZA should be limited to 2.5 mg when coadministered with a strong CYP3A4/5 inhibitor. [See Dosage and Administration (2.3) and Clinical Pharmacology (12.3).]

8 USE IN SPECIFIC POPULATIONS

8.1 Pregnancy

Pregnancy Category B

There are no adequate and well-controlled studies in pregnant women. Because animal reproduction studies are not always predictive of human response, ONGLYZA, like other antidiabetic medications, should be used during pregnancy only if clearly needed.

Saxagliptin was not teratogenic at any dose tested when administered to pregnant rats and rabbits during periods of organogenesis. Incomplete ossification of the pelvis, a form of developmental delay, occurred in rats at a dose of 240 mg/kg, or approximately 1503 and 66 times human exposure to saxagliptin and the active metabolite, respectively, at the maximum recommended human dose (MRHD) of 5 mg. Maternal toxicity and reduced fetal body weights were observed at 7986 and 328 times the human exposure at the MRHD for saxagliptin and the active metabolite, respectively. Minor skeletal variations in rabbits occurred at a maternally toxic dose of 200 mg/kg, or approximately 1432 and 992 times the MRHD.

Coadministration of saxagliptin and metformin, to pregnant rats and rabbits during the period of organogenesis, was neither embryolethal nor teratogenic in either species when tested at doses yielding systemic exposures (AUC) up to 100 and 10 times the MRHD (saxagliptin 5 mg and metformin 2000 mg), respectively, in rats; and 249 and 1.1 times the MRHDs in rabbits. In rats, minor developmental toxicity was limited to an increased incidence of wavy ribs; associated maternal toxicity was limited to weight decrements of 11% to 17% over the course of the study, and related reductions in maternal food consumption. In rabbits, coadministration was poorly tolerated in a subset of mothers (12 of 30), resulting in death, moribundity, or abortion. However, among surviving mothers with evaluable litters, maternal toxicity was limited to marginal reductions in body weight over the course of gestation days 21 to 29; and associated developmental toxicity in these litters was limited to fetal body weight decrements of 7%, and a low incidence of delayed ossification of the fetal hyoid.

Saxagliptin administered to female rats from gestation day 6 to lactation day 20 resulted in decreased body weights in male and female offspring only at maternally toxic doses (exposures ≥1629 and 53 times saxagliptin and its active metabolite at the MRHD). No functional or behavioral toxicity was observed in offspring of rats administered saxagliptin at any dose.

Saxagliptin crosses the placenta into the fetus following dosing in pregnant rats.

8.3 Nursing Mothers

Saxagliptin is secreted in the milk of lactating rats at approximately a 1:1 ratio with plasma drug concentrations. It is not known whether saxagliptin is secreted in human milk. Because many drugs are secreted in human milk, caution should be exercised when ONGLYZA is administered to a nursing woman.

8.4 Pediatric Use

Safety and effectiveness of ONGLYZA in pediatric patients have not been established.

8.5 Geriatric Use

In the six, double-blind, controlled clinical safety and efficacy trials of ONGLYZA, 634 (15.3%) of the 4148 randomized patients were 65 years and over, and 59 (1.4%) patients were 75 years and over. No overall differences in safety or effectiveness were observed between patients ≥65 years old and the younger patients. While this clinical experience has not identified differences in responses between the elderly and younger patients, greater sensitivity of some older individuals cannot be ruled out.

Saxagliptin and its active metabolite are eliminated in part by the kidney. Because elderly patients are more likely to have decreased renal function, care should be taken in dose selection in the elderly based on renal function. [See Dosage and Administration (2.2) and Clinical Pharmacology (12.3).]

10 OVERDOSAGE

In a controlled clinical trial, once-daily, orally-administered ONGLYZA in healthy subjects at doses up to 400 mg daily for 2 weeks (80 times the MRHD) had no dose-related clinical adverse reactions and no clinically meaningful effect on QTc interval or heart rate.

In the event of an overdose, appropriate supportive treatment should be initiated as dictated by the patient’s clinical status. Saxagliptin and its active metabolite are removed by hemodialysis (23% of dose over 4 hours).

11 DESCRIPTION

Saxagliptin is an orally-active inhibitor of the DPP4 enzyme.

Saxagliptin monohydrate is described chemically as (1S,3S,5S)-2-[(2S)-2-Amino-2-(3-hydroxytricyclo[3.3.1.1^3,7]dec-1-yl)acetyl]-2-azabicyclo[3.1.0]hexane-3-carbonitrile, monohydrate or (1S,3S,5S)-2-[(2S)-2-Amino-2-(3-hydroxyadamantan-1-yl)acetyl]-2-azabicyclo[3.1.0]hexane-3-carbonitrile hydrate. The empirical formula is C18H25N3O2•H2O and the molecular weight is 333.43. The structural formula is:

Saxagliptin monohydrate is a white to light yellow or light brown, non-hygroscopic, crystalline powder. It is sparingly soluble in water at 24°C ± 3°C, slightly soluble in ethyl acetate, and soluble in methanol, ethanol, isopropyl alcohol, acetonitrile, acetone, and polyethylene glycol 400 (PEG 400).

Each film-coated tablet of ONGLYZA for oral use contains either 2.79 mg saxagliptin hydrochloride (anhydrous) equivalent to 2.5 mg saxagliptin or 5.58 mg saxagliptin hydrochloride (anhydrous) equivalent to 5 mg saxagliptin and the following inactive ingredients: lactose monohydrate, microcrystalline cellulose, croscarmellose sodium, and magnesium stearate. In addition, the film coating contains the following inactive ingredients: polyvinyl alcohol, polyethylene glycol, titanium dioxide, talc, and iron oxides.

12 CLINICAL PHARMACOLOGY

12.1 Mechanism of Action

Increased concentrations of the incretin hormones such as glucagon-like peptide-1 (GLP-1) and glucose-dependent insulinotropic polypeptide (GIP) are released into the bloodstream from the small intestine in response to meals. These hormones cause insulin release from the pancreatic beta cells in a glucose-dependent manner but are inactivated by the DPP4 enzyme within minutes. GLP-1 also lowers glucagon secretion from pancreatic alpha cells, reducing hepatic glucose production. In patients with type 2 diabetes, concentrations of GLP-1 are reduced but the insulin response to GLP-1 is preserved. Saxagliptin is a competitive DPP4 inhibitor that slows the inactivation of the incretin hormones, thereby increasing their bloodstream concentrations and reducing fasting and postprandial glucose concentrations in a glucose-dependent manner in patients with type 2 diabetes mellitus.

12.2 Pharmacodynamics

In patients with type 2 diabetes mellitus, administration of ONGLYZA inhibits DPP4 enzyme activity for a 24-hour period. After an oral glucose load or a meal, this DPP4 inhibition resulted in a 2- to 3-fold increase in circulating levels of active GLP-1 and GIP, decreased glucagon concentrations, and increased glucose-dependent insulin secretion from pancreatic beta cells. The rise in insulin and decrease in glucagon were associated with lower fasting glucose concentrations and reduced glucose excursion following an oral glucose load or a meal.

Cardiac Electrophysiology

In a randomized, double-blind, placebo-controlled, 4-way crossover, active comparator study using moxifloxacin in 40 healthy subjects, ONGLYZA was not associated with clinically meaningful prolongation of the QTc interval or heart rate at daily doses up to 40 mg (8 times the MRHD).

12.3 Pharmacokinetics

The pharmacokinetics of saxagliptin and its active metabolite, 5-hydroxy saxagliptin were similar in healthy subjects and in patients with type 2 diabetes mellitus. The Cmax and AUC values of saxagliptin and its active metabolite increased proportionally in the 2.5 to 400 mg dose range. Following a 5 mg single oral dose of saxagliptin to healthy subjects, the mean plasma AUC values for saxagliptin and its active metabolite were 78 ng•h/mL and 214 ng•h/mL, respectively. The corresponding plasma Cmax values were 24 ng/mL and 47 ng/mL, respectively. The average variability (%CV) for AUC and Cmax for both saxagliptin and its active metabolite was less than 25%.

No appreciable accumulation of either saxagliptin or its active metabolite was observed with repeated once-daily dosing at any dose level. No dose- and time-dependence were observed in the clearance of saxagliptin and its active metabolite over 14 days of once-daily dosing with saxagliptin at doses ranging from 2.5 to 400 mg.

Absorption

The median time to maximum concentration (Tmax) following the 5 mg once daily dose was 2 hours for saxagliptin and 4 hours for its active metabolite. Administration with a high-fat meal resulted in an increase in Tmax of saxagliptin by approximately 20 minutes as compared to fasted conditions. There was a 27% increase in the AUC of saxagliptin when given with a meal as compared to fasted conditions. ONGLYZA may be administered with or without food.

Distribution

The in vitro protein binding of saxagliptin and its active metabolite in human serum is negligible. Therefore, changes in blood protein levels in various disease states (e.g., renal or hepatic impairment) are not expected to alter the disposition of saxagliptin.

Metabolism

The metabolism of saxagliptin is primarily mediated by cytochrome P450 3A4/5 (CYP3A4/5). The major metabolite of saxagliptin is also a DPP4 inhibitor, which is one-half as potent as saxagliptin. Therefore, strong CYP3A4/5 inhibitors and inducers will alter the pharmacokinetics of saxagliptin and its active metabolite. [See Drug Interactions (7).]

Excretion

Saxagliptin is eliminated by both renal and hepatic pathways. Following a single 50 mg dose of ^14C-saxagliptin, 24%, 36%, and 75% of the dose was excreted in the urine as saxagliptin, its active metabolite, and total radioactivity, respectively. The average renal clearance of saxagliptin (~230 mL/min) was greater than the average estimated glomerular filtration rate (~120 mL/min), suggesting some active renal excretion. A total of 22% of the administered radioactivity was recovered in feces representing the fraction of the saxagliptin dose excreted in bile and/or unabsorbed drug from the gastrointestinal tract. Following a single oral dose of ONGLYZA 5 mg to healthy subjects, the mean plasma terminal half-life (t1/2) for saxagliptin and its active metabolite was 2.5 and 3.1 hours, respectively.

Specific Populations

Renal Impairment

A single-dose, open-label study was conducted to evaluate the pharmacokinetics of saxagliptin (10 mg dose) in subjects with varying degrees of chronic renal impairment (N=8 per group) compared to subjects with normal renal function. The study included patients with renal impairment classified on the basis of creatinine clearance as mild (>50 to ≤80 mL/min), moderate (30 to ≤50 mL/min), and severe (<30 mL/min), as well as patients with end-stage renal disease on hemodialysis. Creatinine clearance was estimated from serum creatinine based on the Cockcroft-Gault formula:

CrCl = | [140 − age (years)] × weight (kg) | {× 0.85 for female patients}
 | [72 × serum creatinine (mg/dL)]

The degree of renal impairment did not affect the Cmax of saxagliptin or its active metabolite. In subjects with mild renal impairment, the AUC values of saxagliptin and its active metabolite were 20% and 70% higher, respectively, than AUC values in subjects with normal renal function. Because increases of this magnitude are not considered to be clinically relevant, dosage adjustment in patients with mild renal impairment is not recommended. In subjects with moderate or severe renal impairment, the AUC values of saxagliptin and its active metabolite were up to 2.1- and 4.5-fold higher, respectively, than AUC values in subjects with normal renal function. To achieve plasma exposures of saxagliptin and its active metabolite similar to those in patients with normal renal function, the recommended dose is 2.5 mg once daily in patients with moderate and severe renal impairment, as well as in patients with end-stage renal disease requiring hemodialysis. Saxagliptin is removed by hemodialysis.

Hepatic Impairment

In subjects with hepatic impairment (Child-Pugh classes A, B, and C), mean Cmax and AUC of saxagliptin were up to 8% and 77% higher, respectively, compared to healthy matched controls following administration of a single 10 mg dose of saxagliptin. The corresponding Cmax and AUC of the active metabolite were up to 59% and 33% lower, respectively, compared to healthy matched controls. These differences are not considered to be clinically meaningful. No dosage adjustment is recommended for patients with hepatic impairment.

Body Mass Index

No dosage adjustment is recommended based on body mass index (BMI) which was not identified as a significant covariate on the apparent clearance of saxagliptin or its active metabolite in the population pharmacokinetic analysis.

Gender

No dosage adjustment is recommended based on gender. There were no differences observed in saxagliptin pharmacokinetics between males and females. Compared to males, females had approximately 25% higher exposure values for the active metabolite than males, but this difference is unlikely to be of clinical relevance. Gender was not identified as a significant covariate on the apparent clearance of saxagliptin and its active metabolite in the population pharmacokinetic analysis.

Geriatric

No dosage adjustment is recommended based on age alone. Elderly subjects (65-80 years) had 23% and 59% higher geometric mean Cmax and geometric mean AUC values, respectively, for saxagliptin than young subjects (18-40 years). Differences in active metabolite pharmacokinetics between elderly and young subjects generally reflected the differences observed in saxagliptin pharmacokinetics. The difference between the pharmacokinetics of saxagliptin and the active metabolite in young and elderly subjects is likely due to multiple factors including declining renal function and metabolic capacity with increasing age. Age was not identified as a significant covariate on the apparent clearance of saxagliptin and its active metabolite in the population pharmacokinetic analysis.

Pediatric

Studies characterizing the pharmacokinetics of saxagliptin in pediatric patients have not been performed.

Race and Ethnicity

No dosage adjustment is recommended based on race. The population pharmacokinetic analysis compared the pharmacokinetics of saxagliptin and its active metabolite in 309 Caucasian subjects with 105 non-Caucasian subjects (consisting of six racial groups). No significant difference in the pharmacokinetics of saxagliptin and its active metabolite were detected between these two populations.

Drug-Drug Interactions

In Vitro Assessment of Drug Interactions

The metabolism of saxagliptin is primarily mediated by CYP3A4/5.

In in vitro studies, saxagliptin and its active metabolite did not inhibit CYP1A2, 2A6, 2B6, 2C9, 2C19, 2D6, 2E1, or 3A4, or induce CYP1A2, 2B6, 2C9, or 3A4. Therefore, saxagliptin is not expected to alter the metabolic clearance of coadministered drugs that are metabolized by these enzymes. Saxagliptin is a P-glycoprotein (P-gp) substrate but is not a significant inhibitor or inducer of P-gp.

In Vivo Assessment of Drug Interactions

Table 3: Effect of Coadministered Drugs on Systemic Exposures of Saxagliptin and its Active Metabolite, 5-hydroxy Saxagliptin
Coadministered Drug | Dose of Coadministered Drug* | Dosing of Saxagliptin* | Geometric Mean Ratio (ratio with/without coadministered drug) No Effect = 1.00
 |  |  |  | AUC† | Cmax
No dosing adjustments required for the following:
Metformin | 1000 mg | 100 mg | saxagliptin 5-hydroxy saxagliptin | 0.98 0.99 | 0.79 0.88
Glyburide | 5 mg | 10 mg | saxagliptin 5-hydroxy saxagliptin | 0.98 ND | 1.08 ND
Pioglitazone‡ | 45 mg QD for 10 days | 10 mg QD for 5 days | saxagliptin 5-hydroxy saxagliptin | 1.11 ND | 1.11 ND
Digoxin | 0.25 mg q6h first day followed by q12h second day followed by QD for 5 days | 10 mg QD for 7 days | saxagliptin 5-hydroxy saxagliptin | 1.05 1.06 | 0.99 1.02
Simvastatin | 40 mg QD for 8 days | 10 mg QD for 4 days | saxagliptin 5-hydroxy saxagliptin | 1.12 1.02 | 1.21 1.08
Diltiazem | 360 mg LA QD for 9 days | 10 mg | saxagliptin 5-hydroxy saxagliptin | 2.09 0.66 | 1.63 0.57
Rifampin§ | 600 mg QD for 6 days | 5 mg | saxagliptin 5-hydroxy saxagliptin | 0.24 1.03 | 0.47 1.39
Omeprazole | 40 mg QD for 5 days | 10 mg | saxagliptin 5-hydroxy saxagliptin | 1.13 ND | 0.98 ND
Aluminum hydroxide + magnesium hydroxide + simethicone | aluminum hydroxide: 2400 mg magnesium hydroxide: 2400 mg simethicone: 240 mg | 10 mg | saxagliptin 5-hydroxy saxagliptin | 0.97 ND | 0.74 ND
Famotidine | 40 mg | 10 mg | saxagliptin 5-hydroxy saxagliptin | 1.03 ND | 1.14 ND
Limit ONGLYZA dose to 2.5 mg once daily when coadministered with strong CYP3A4/5 inhibitors:
Ketoconazole | 200 mg BID for 9 days | 100 mg | saxagliptin 5-hydroxy saxagliptin | 2.45 0.12 | 1.62 0.05
Ketoconazole | 200 mg BID for 7 days | 20 mg | saxagliptin 5-hydroxy saxagliptin | 3.67 ND | 2.44 ND
* Single dose unless otherwise noted
† AUC = AUC(INF) for drugs given as single dose and AUC = AUC(TAU) for drugs given in multiple doses
‡ Results exclude one subject
§ The plasma dipeptidyl peptidase-4 (DPP4) activity inhibition over a 24-hour dose interval was not affected by rifampin.
ND=not determined; QD=once daily; q6h=every 6 hours; q12h=every 12 hours; BID=twice daily; LA=long acting

Table 4: Effect of Saxagliptin on Systemic Exposures of Coadministered Drugs
Coadministered Drug | Dose of Coadministered Drug* | Dosing of Saxagliptin* | Geometric Mean Ratio (ratio with/without saxagliptin) No Effect = 1.00
 |  |  |  | AUC† | Cmax
No dosing adjustments required for the following:
Metformin | 1000 mg | 100 mg | metformin | 1.20 | 1.09
Glyburide | 5 mg | 10 mg | glyburide | 1.06 | 1.16
Pioglitazone‡ | 45 mg QD for 10 days | 10 mg QD for 5 days | pioglitazone hydroxy-pioglitazone | 1.08 ND | 1.14 ND
Digoxin | 0.25 mg q6h first day followed by q12h second day followed by QD for 5 days | 10 mg QD for 7 days | digoxin | 1.06 | 1.09
Simvastatin | 40 mg QD for 8 days | 10 mg QD for 4 days | simvastatin simvastatin acid | 1.04 1.16 | 0.88 1.00
Diltiazem | 360 mg LA QD for 9 days | 10 mg | diltiazem | 1.10 | 1.16
Ketoconazole | 200 mg BID for 9 days | 100 mg | ketoconazole | 0.87 | 0.84
Ethinyl estradiol and Norgestimate | ethinyl estradiol 0.035 mg and norgestimate 0.250 mg for 21 days | 5 mg QD for 21 days | ethinyl estradiol norelgestromin norgestrel | 1.07 1.10 1.13 | 0.98 1.09 1.17
* Single dose unless otherwise noted
† AUC = AUC(INF) for drugs given as single dose and AUC = AUC(TAU) for drugs given in multiple doses
‡ Results include all subjects
ND=not determined; QD=once daily; q6h=every 6 hours; q12h=every 12 hours; BID=twice daily; LA=long acting

13 NONCLINICAL TOXICOLOGY

13.1 Carcinogenesis, Mutagenesis, Impairment of Fertility

Saxagliptin did not induce tumors in either mice (50, 250, and 600 mg/kg) or rats (25, 75, 150, and 300 mg/kg) at the highest doses evaluated. The highest doses evaluated in mice were equivalent to approximately 870 (males) and 1165 (females) times the human exposure at the MRHD of 5 mg/day. In rats, exposures were approximately 355 (males) and 2217 (females) times the MRHD.

Saxagliptin was not mutagenic or clastogenic with or without metabolic activation in an in vitro Ames bacterial assay, an in vitro cytogenetics assay in primary human lymphocytes, an in vivo oral micronucleus assay in rats, an in vivo oral DNA repair study in rats, and an oral in vivo/in vitro cytogenetics study in rat peripheral blood lymphocytes. The active metabolite was not mutagenic in an in vitro Ames bacterial assay.

In a rat fertility study, males were treated with oral gavage doses for 2 weeks prior to mating, during mating, and up to scheduled termination (approximately 4 weeks total) and females were treated with oral gavage doses for 2 weeks prior to mating through gestation day 7. No adverse effects on fertility were observed at exposures of approximately 603 (males) and 776 (females) times the MRHD. Higher doses that elicited maternal toxicity also increased fetal resorptions (approximately 2069 and 6138 times the MRHD). Additional effects on estrous cycling, fertility, ovulation, and implantation were observed at approximately 6138 times the MRHD.

13.2 Animal Toxicology

Saxagliptin produced adverse skin changes in the extremities of cynomolgus monkeys (scabs and/or ulceration of tail, digits, scrotum, and/or nose). Skin lesions were reversible at ≥20 times the MRHD but in some cases were irreversible and necrotizing at higher exposures. Adverse skin changes were not observed at exposures similar to (1 to 3 times) the MRHD of 5 mg. Clinical correlates to skin lesions in monkeys have not been observed in human clinical trials of saxagliptin.

14 CLINICAL STUDIES

ONGLYZA has been studied as monotherapy and in combination with metformin, glyburide, and thiazolidinedione (pioglitazone and rosiglitazone) therapy.

A total of 4148 patients with type 2 diabetes mellitus were randomized in six, double-blind, controlled clinical trials conducted to evaluate the safety and glycemic efficacy of ONGLYZA. A total of 3021 patients in these trials were treated with ONGLYZA. In these trials, the mean age was 54 years, and 71% of patients were Caucasian, 16% were Asian, 4% were black, and 9% were of other racial groups. An additional 423 patients, including 315 who received ONGLYZA, participated in a placebo-controlled, dose-ranging study of 6 to 12 weeks in duration.

In these six, double-blind trials, ONGLYZA was evaluated at doses of 2.5 mg and 5 mg once daily. Three of these trials also evaluated a saxagliptin dose of 10 mg daily. The 10 mg daily dose of saxagliptin did not provide greater efficacy than the 5 mg daily dose. Treatment with ONGLYZA at all doses produced clinically relevant and statistically significant improvements in hemoglobin A1c (A1C), fasting plasma glucose (FPG), and 2-hour postprandial glucose (PPG) following a standard oral glucose tolerance test (OGTT), compared to control. Reductions in A1C were seen across subgroups including gender, age, race, and baseline BMI.

ONGLYZA was not associated with significant changes from baseline in body weight or fasting serum lipids compared to placebo.

ONGLYZA has also been evaluated in three additional trials in patients with type 2 diabetes: an active-controlled trial comparing add-on therapy with ONGLYZA to glipizide in 858 patients inadequately controlled on metformin alone, a trial comparing ONGLYZA to placebo in 455 patients inadequately controlled on insulin alone or on insulin in combination with metformin, and a trial comparing ONGLYZA to placebo in 170 patients with type 2 diabetes and moderate or severe renal impairment or ESRD.

14.1 Monotherapy

A total of 766 patients with type 2 diabetes inadequately controlled on diet and exercise (A1C ≥7% to ≤10%) participated in two 24-week, double-blind, placebo-controlled trials evaluating the efficacy and safety of ONGLYZA monotherapy.

In the first trial, following a 2-week single-blind diet, exercise, and placebo lead-in period, 401 patients were randomized to 2.5 mg, 5 mg, or 10 mg of ONGLYZA or placebo. Patients who failed to meet specific glycemic goals during the study were treated with metformin rescue therapy, added on to placebo or ONGLYZA. Efficacy was evaluated at the last measurement prior to rescue therapy for patients needing rescue. Dose titration of ONGLYZA was not permitted.

Treatment with ONGLYZA 2.5 mg and 5 mg daily provided significant improvements in A1C, FPG, and PPG compared to placebo (Table 5). The percentage of patients who discontinued for lack of glycemic control or who were rescued for meeting prespecified glycemic criteria was 16% in the ONGLYZA 2.5 mg treatment group, 20% in the ONGLYZA 5 mg treatment group, and 26% in the placebo group.

Table 5: Glycemic Parameters at Week 24 in a Placebo-Controlled Study of ONGLYZA Monotherapy in Patients with Type 2 Diabetes*
Efficacy Parameter | ONGLYZA 2.5 mg N=102 | ONGLYZA 5 mg N=106 | Placebo N=95
Hemoglobin A1C (%) | N=100 | N=103 | N=92
Baseline (mean) | 7.9 | 8.0 | 7.9
Change from baseline (adjusted mean†) | −0.4 | −0.5 | +0.2
Difference from placebo (adjusted mean†) | −0.6‡ | −0.6‡
95% Confidence Interval | (−0.9, −0.3) | (−0.9, −0.4)
Percent of patients achieving A1C <7% | 35% (35/100) | 38%§ (39/103) | 24% (22/92)
Fasting Plasma Glucose (mg/dL) | N=101 | N=105 | N=92
Baseline (mean) | 178 | 171 | 172
Change from baseline (adjusted mean†) | −15 | −9 | +6
Difference from placebo (adjusted mean†) | −21§ | −15§
95% Confidence Interval | (−31, −10) | (−25, −4)
2-hour Postprandial Glucose (mg/dL) | N=78 | N=84 | N=71
Baseline (mean) | 279 | 278 | 283
Change from baseline (adjusted mean†) | −45 | −43 | −6
Difference from placebo (adjusted mean†) | −39¶ | −37§
95% Confidence Interval | (−61, −16) | (−59, −15)
* Intent-to-treat population using last observation on study or last observation prior to metformin rescue therapy for patients needing rescue.
† Least squares mean adjusted for baseline value.
‡ p-value <0.0001 compared to placebo
§ p-value <0.05 compared to placebo
¶ Significance was not tested for the 2-hour PPG for the 2.5 mg dose of ONGLYZA.

A second 24-week monotherapy trial was conducted to assess a range of dosing regimens for ONGLYZA. Treatment-naive patients with inadequately controlled diabetes (A1C ≥7% to ≤10%) underwent a 2-week, single-blind diet, exercise, and placebo lead-in period. A total of 365 patients were randomized to 2.5 mg every morning, 5 mg every morning, 2.5 mg with possible titration to 5 mg every morning, or 5 mg every evening of ONGLYZA, or placebo. Patients who failed to meet specific glycemic goals during the study were treated with metformin rescue therapy added on to placebo or ONGLYZA; the number of patients randomized per treatment group ranged from 71 to 74.

Treatment with either ONGLYZA 5 mg every morning or 5 mg every evening provided significant improvements in A1C versus placebo (mean placebo-corrected reductions of −0.4% and −0.3%, respectively). Treatment with ONGLYZA 2.5 mg every morning also provided significant improvement in A1C versus placebo (mean placebo-corrected reduction of −0.4%).

14.2 Combination Therapy

Add-On Combination Therapy with Metformin

A total of 743 patients with type 2 diabetes participated in this 24-week, randomized, double-blind, placebo-controlled trial to evaluate the efficacy and safety of ONGLYZA in combination with metformin in patients with inadequate glycemic control (A1C ≥7% and ≤10%) on metformin alone. To qualify for enrollment, patients were required to be on a stable dose of metformin (1500-2550 mg daily) for at least 8 weeks.

Patients who met eligibility criteria were enrolled in a single-blind, 2-week, dietary and exercise placebo lead-in period during which patients received metformin at their pre-study dose, up to 2500 mg daily. Following the lead-in period, eligible patients were randomized to 2.5 mg, 5 mg, or 10 mg of ONGLYZA or placebo in addition to their current dose of open-label metformin. Patients who failed to meet specific glycemic goals during the study were treated with pioglitazone rescue therapy, added on to existing study medications. Dose titrations of ONGLYZA and metformin were not permitted.

ONGLYZA 2.5 mg and 5 mg add-on to metformin provided significant improvements in A1C, FPG, and PPG compared with placebo add-on to metformin (Table 6). Mean changes from baseline for A1C over time and at endpoint are shown in Figure 1. The proportion of patients who discontinued for lack of glycemic control or who were rescued for meeting prespecified glycemic criteria was 15% in the ONGLYZA 2.5 mg add-on to metformin group, 13% in the ONGLYZA 5 mg add-on to metformin group, and 27% in the placebo add-on to metformin group.

Table 6: Glycemic Parameters at Week 24 in a Placebo-Controlled Study of ONGLYZA as Add-On Combination Therapy with Metformin*
Efficacy Parameter | ONGLYZA 2.5 mg + Metformin N=192 | ONGLYZA 5 mg + Metformin N=191 | Placebo + Metformin N=179
Hemoglobin A1C (%) | N=186 | N=186 | N=175
Baseline (mean) | 8.1 | 8.1 | 8.1
Change from baseline (adjusted mean†) | −0.6 | −0.7 | +0.1
Difference from placebo (adjusted mean†) | −0.7‡ | −0.8‡
95% Confidence Interval | (−0.9, −0.5) | (−1.0, −0.6)
Percent of patients achieving A1C <7% | 37%§ (69/186) | 44%§ (81/186) | 17% (29/175)
Fasting Plasma Glucose (mg/dL) | N=188 | N=187 | N=176
Baseline (mean) | 174 | 179 | 175
Change from baseline (adjusted mean†) | −14 | −22 | +1
Difference from placebo (adjusted mean†) | −16§ | −23§
95% Confidence Interval | (−23, −9) | (−30, −16)
2-hour Postprandial Glucose (mg/dL) | N=155 | N=155 | N=135
Baseline (mean) | 294 | 296 | 295
Change from baseline (adjusted mean†) | −62 | −58 | −18
Difference from placebo (adjusted mean†) | −44§ | −40§
95% Confidence Interval | (−60, −27) | (−56, −24)
* Intent-to-treat population using last observation on study or last observation prior to pioglitazone rescue therapy for patients needing rescue.
† Least squares mean adjusted for baseline value.
‡ p-value <0.0001 compared to placebo + metformin
§ p-value <0.05 compared to placebo + metformin

Figure 1: Mean Change from Baseline in A1C in a Placebo-Controlled Trial of ONGLYZA as Add-On Combination Therapy with Metformin*

* Includes patients with a baseline and week 24 value.
Week 24 (LOCF) includes intent-to-treat population using last observation on study prior to pioglitazone rescue therapy for patients needing rescue. Mean change from baseline is adjusted for baseline value.

Add-On Combination Therapy with a Thiazolidinedione

A total of 565 patients with type 2 diabetes participated in this 24-week, randomized, double-blind, placebo-controlled trial to evaluate the efficacy and safety of ONGLYZA in combination with a thiazolidinedione (TZD) in patients with inadequate glycemic control (A1C ≥7% to ≤10.5%) on TZD alone. To qualify for enrollment, patients were required to be on a stable dose of pioglitazone (30-45 mg once daily) or rosiglitazone (4 mg once daily or 8 mg either once daily or in two divided doses of 4 mg) for at least 12 weeks.

Patients who met eligibility criteria were enrolled in a single-blind, 2-week, dietary and exercise placebo lead-in period during which patients received TZD at their pre-study dose. Following the lead-in period, eligible patients were randomized to 2.5 mg or 5 mg of ONGLYZA or placebo in addition to their current dose of TZD. Patients who failed to meet specific glycemic goals during the study were treated with metformin rescue, added on to existing study medications. Dose titration of ONGLYZA or TZD was not permitted during the study. A change in TZD regimen from rosiglitazone to pioglitazone at specified, equivalent therapeutic doses was permitted at the investigator’s discretion if believed to be medically appropriate.

ONGLYZA 2.5 mg and 5 mg add-on to TZD provided significant improvements in A1C, FPG, and PPG compared with placebo add-on to TZD (Table 7). The proportion of patients who discontinued for lack of glycemic control or who were rescued for meeting prespecified glycemic criteria was 10% in the ONGLYZA 2.5 mg add-on to TZD group, 6% for the ONGLYZA 5 mg add-on to TZD group, and 10% in the placebo add-on to TZD group.

Table 7: Glycemic Parameters at Week 24 in a Placebo-Controlled Study of ONGLYZA as Add-On Combination Therapy with a Thiazolidinedione*
Efficacy Parameter | ONGLYZA 2.5 mg + TZD N=195 | ONGLYZA 5 mg + TZD N=186 | Placebo + TZD N=184
Hemoglobin A1C (%) | N=192 | N=183 | N=180
Baseline (mean) | 8.3 | 8.4 | 8.2
Change from baseline (adjusted mean†) | −0.7 | −0.9 | −0.3
Difference from placebo (adjusted mean†) | −0.4§ | −0.6‡
95% Confidence Interval | (−0.6, −0.2) | (−0.8, −0.4)
Percent of patients achieving A1C <7% | 42%§ (81/192) | 42%§ (77/184) | 26% (46/180)
Fasting Plasma Glucose (mg/dL) | N=193 | N=185 | N=181
Baseline (mean) | 163 | 160 | 162
Change from baseline (adjusted mean†) | −14 | −17 | −3
Difference from placebo (adjusted mean†) | −12§ | −15§
95% Confidence Interval | (−20, −3) | (−23, −6)
2-hour Postprandial Glucose (mg/dL) | N=156 | N=134 | N=127
Baseline (mean) | 296 | 303 | 291
Change from baseline (adjusted mean†) | −55 | −65 | −15
Difference from placebo (adjusted mean†) | −40§ | −50§
95% Confidence Interval | (−56, −24) | (−66, −34)
* Intent-to-treat population using last observation on study or last observation prior to metformin rescue therapy for patients needing rescue.
† Least squares mean adjusted for baseline value.
‡ p-value <0.0001 compared to placebo + TZD
§ p-value <0.05 compared to placebo + TZD

Add-On Combination Therapy with Glyburide

A total of 768 patients with type 2 diabetes participated in this 24-week, randomized, double-blind, placebo-controlled trial to evaluate the efficacy and safety of ONGLYZA in combination with a sulfonylurea (SU) in patients with inadequate glycemic control at enrollment (A1C ≥7.5% to ≤10%) on a submaximal dose of SU alone. To qualify for enrollment, patients were required to be on a submaximal dose of SU for 2 months or greater. In this study, ONGLYZA in combination with a fixed, intermediate dose of SU was compared to titration to a higher dose of SU.

Patients who met eligibility criteria were enrolled in a single-blind, 4-week, dietary and exercise lead-in period, and placed on glyburide 7.5 mg once daily. Following the lead-in period, eligible patients with A1C ≥7% to ≤10% were randomized to either 2.5 mg or 5 mg of ONGLYZA add-on to 7.5 mg glyburide or to placebo plus a 10 mg total daily dose of glyburide. Patients who received placebo were eligible to have glyburide up-titrated to a total daily dose of 15 mg. Up-titration of glyburide was not permitted in patients who received ONGLYZA 2.5 mg or 5 mg. Glyburide could be down-titrated in any treatment group once during the 24-week study period due to hypoglycemia as deemed necessary by the investigator. Approximately 92% of patients in the placebo plus glyburide group were up-titrated to a final total daily dose of 15 mg during the first 4 weeks of the study period. Patients who failed to meet specific glycemic goals during the study were treated with metformin rescue, added on to existing study medication. Dose titration of ONGLYZA was not permitted during the study.

In combination with glyburide, ONGLYZA 2.5 mg and 5 mg provided significant improvements in A1C, FPG, and PPG compared with the placebo plus up-titrated glyburide group (Table 8). The proportion of patients who discontinued for lack of glycemic control or who were rescued for meeting prespecified glycemic criteria was 18% in the ONGLYZA 2.5 mg add-on to glyburide group, 17% in the ONGLYZA 5 mg add-on to glyburide group, and 30% in the placebo plus up-titrated glyburide group.

Table 8: Glycemic Parameters at Week 24 in a Placebo-Controlled Study of ONGLYZA as Add-On Combination Therapy with Glyburide*
Efficacy Parameter | ONGLYZA 2.5 mg + Glyburide 7.5 mg N=248 | ONGLYZA 5 mg + Glyburide 7.5 mg N=253 | Placebo + Up-Titrated Glyburide N=267
Hemoglobin A1C (%) | N=246 | N=250 | N=264
Baseline (mean) | 8.4 | 8.5 | 8.4
Change from baseline (adjusted mean†) | −0.5 | −0.6 | +0.1
Difference from up-titrated glyburide (adjusted mean†) | −0.6‡ | −0.7‡
95% Confidence Interval | (−0.8, −0.5) | (−0.9, −0.6)
Percent of patients achieving A1C <7% | 22%§ (55/246) | 23%§ (57/250) | 9% (24/264)
Fasting Plasma Glucose (mg/dL) | N=247 | N=252 | N=265
Baseline (mean) | 170 | 175 | 174
Change from baseline (adjusted mean†) | −7 | −10 | +1
Difference from up-titrated glyburide (adjusted mean†) | −8§ | −10§
95% Confidence Interval | (−14, −1) | (−17, −4)
2-hour Postprandial Glucose (mg/dL) | N=195 | N=202 | N=206
Baseline (mean) | 309 | 315 | 323
Change from baseline (adjusted mean†) | −31 | −34 | +8
Difference from up-titrated glyburide (adjusted mean†) | −38§ | −42§
95% Confidence Interval | (−50, −27) | (−53, −31)
* Intent-to-treat population using last observation on study or last observation prior to metformin rescue therapy for patients needing rescue.
† Least squares mean adjusted for baseline value.
‡ p-value <0.0001 compared to placebo + up-titrated glyburide
§ p-value <0.05 compared to placebo + up-titrated glyburide

Coadministration with Metformin in Treatment-Naive Patients

A total of 1306 treatment-naive patients with type 2 diabetes mellitus participated in this 24-week, randomized, double-blind, active-controlled trial to evaluate the efficacy and safety of ONGLYZA coadministered with metformin in patients with inadequate glycemic control (A1C ≥8% to ≤12%) on diet and exercise alone. Patients were required to be treatment-naive to be enrolled in this study.

Patients who met eligibility criteria were enrolled in a single-blind, 1-week, dietary and exercise placebo lead-in period. Patients were randomized to one of four treatment arms: ONGLYZA 5 mg + metformin 500 mg, saxagliptin 10 mg + metformin 500 mg, saxagliptin 10 mg + placebo, or metformin 500 mg + placebo. ONGLYZA was dosed once daily. In the 3 treatment groups using metformin, the metformin dose was up-titrated weekly in 500 mg per day increments, as tolerated, to a maximum of 2000 mg per day based on FPG. Patients who failed to meet specific glycemic goals during the studies were treated with pioglitazone rescue as add-on therapy.

Coadministration of ONGLYZA 5 mg plus metformin provided significant improvements in A1C, FPG, and PPG compared with placebo plus metformin (Table 9).

Table 9: Glycemic Parameters at Week 24 in a Placebo-Controlled Trial of ONGLYZA Coadministration with Metformin in Treatment-Naive Patients*
Efficacy Parameter | ONGLYZA 5 mg + Metformin N=320 | Placebo + Metformin N=328
Hemoglobin A1C (%) | N=306 | N=313
Baseline (mean) | 9.4 | 9.4
Change from baseline (adjusted mean†) | −2.5 | −2.0
Difference from placebo + metformin (adjusted mean†) | −0.5‡
95% Confidence Interval | (−0.7, −0.4)
Percent of patients achieving A1C <7% | 60%§ (185/307) | 41% (129/314)
Fasting Plasma Glucose (mg/dL) | N=315 | N=320
Baseline (mean) | 199 | 199
Change from baseline (adjusted mean†) | −60 | −47
Difference from placebo + metformin (adjusted mean†) | −13§
95% Confidence Interval | (−19, −6)
2-hour Postprandial Glucose (mg/dL) | N=146 | N=141
Baseline (mean) | 340 | 355
Change from baseline (adjusted mean†) | −138 | −97
Difference from placebo + metformin (adjusted mean†) | −41§
95% Confidence Interval | (−57, −25)
* Intent-to-treat population using last observation on study or last observation prior to pioglitazone rescue therapy for patients needing rescue.
† Least squares mean adjusted for baseline value.
‡ p-value <0.0001 compared to placebo + metformin
§ p-value <0.05 compared to placebo + metformin

Add-On Combination Therapy with Metformin versus Glipizide Add-On Combination Therapy with Metformin

In this 52-week, active-controlled trial, a total of 858 patients with type 2 diabetes and inadequate glycemic control (A1C >6.5% and ≤10%) on metformin alone were randomized to double-blind add-on therapy with ONGLYZA or glipizide. Patients were required to be on a stable dose of metformin (at least 1500 mg daily) for at least 8 weeks prior to enrollment.

Patients who met eligibility criteria were enrolled in a single-blind, 2-week, dietary and exercise placebo lead-in period during which patients received metformin (1500-3000 mg based on their pre-study dose). Following the lead-in period, eligible patients were randomized to 5 mg of ONGLYZA or 5 mg of glipizide in addition to their current dose of open-label metformin. Patients in the glipizide plus metformin group underwent blinded titration of the glipizide dose during the first 18 weeks of the trial up to a maximum glipizide dose of 20 mg per day. Titration was based on a goal FPG ≤110 mg/dL or the highest tolerable glipizide dose. Fifty percent (50%) of the glipizide-treated patients were titrated to the 20-mg daily dose; 21% of the glipizide-treated patients had a final daily glipizide dose of 5 mg or less. The mean final daily dose of glipizide was 15 mg.

After 52 weeks of treatment, ONGLYZA and glipizide resulted in similar mean reductions from baseline in A1C when added to metformin therapy (Table 10). This conclusion may be limited to patients with baseline A1C comparable to those in the trial (91% of patients had baseline A1C <9%).

From a baseline mean body weight of 89 kg, there was a statistically significant mean reduction of 1.1 kg in patients treated with ONGLYZA compared to a mean weight gain of 1.1 kg in patients treated with glipizide (p<0.0001).

Table 10: Glycemic Parameters at Week 52 in an Active-Controlled Trial of ONGLYZA versus Glipizide in Combination with Metformin*
Efficacy Parameter | ONGLYZA 5 mg + Metformin N=428 | Titrated Glipizide + Metformin N=430
Hemoglobin A1C (%) | N=423 | N=423
Baseline (mean) | 7.7 | 7.6
Change from baseline (adjusted mean†) | −0.6 | −0.7
Difference from glipizide + metformin (adjusted mean†) | 0.1
95% Confidence Interval | (−0.02, 0.2)‡
Fasting Plasma Glucose (mg/dL) | N=420 | N=420
Baseline (mean) | 162 | 161
Change from baseline (adjusted mean†) | −9 | −16
Difference from glipizide + metformin (adjusted mean†) | 6
95% Confidence Interval | (2, 11)§
* Intent-to-treat population using last observation on study.
† Least squares mean adjusted for baseline value.
‡ Saxagliptin + metformin is considered non-inferior to glipizide + metformin because the upper limit of this confidence interval is less than the prespecified non-inferiority margin of 0.35%.
§ Significance not tested.

Add-On Combination Therapy with Insulin (with or without metformin)

A total of 455 patients with type 2 diabetes participated in this 24-week, randomized, double-blind, placebo-controlled trial to evaluate the efficacy and safety of ONGLYZA in combination with insulin in patients with inadequate glycemic control (A1C ≥7.5% and ≤11%) on insulin alone (N=141) or on insulin in combination with a stable dose of metformin (N=314). Patients were required to be on a stable dose of insulin (≥30 units to ≤150 units daily) with ≤20% variation in total daily dose for ≥8 weeks prior to screening. Patients entered the trial on intermediate- or long-acting (basal) insulin or premixed insulin. Patients using short-acting insulins were excluded unless the short-acting insulin was administered as part of a premixed insulin.

Patients who met eligibility criteria were enrolled in a single-blind, four-week, dietary and exercise placebo lead-in period during which patients received insulin (and metformin if applicable) at their pretrial dose(s). Following the lead-in period, eligible patients were randomized to add-on therapy with either ONGLYZA 5 mg or placebo. Doses of the antidiabetic therapies were to remain stable but patients were rescued and allowed to adjust the insulin regimen if specific glycemic goals were not met or if the investigator learned that the patient had self-increased the insulin dose by >20%. Data after rescue were excluded from the primary efficacy analyses.

Add-on therapy with ONGLYZA 5 mg provided significant improvements from baseline to Week 24 in A1C and PPG compared with add-on placebo (Table 11). Similar mean reductions in A1C versus placebo were observed for patients using ONGLYZA 5 mg add-on to insulin alone and ONGLYZA 5 mg add-on to insulin in combination with metformin (−0.4% and −0.4%, respectively). The percentage of patients who discontinued for lack of glycemic control or who were rescued was 23% in the ONGLYZA group and 32% in the placebo group.

The mean daily insulin dose at baseline was 53 units in patients treated with ONGLYZA 5 mg and 55 units in patients treated with placebo. The mean change from baseline in daily dose of insulin was 2 units for the ONGLYZA 5 mg group and 5 units for the placebo group.

Table 11: Glycemic Parameters at Week 24 in a Placebo-Controlled Trial of ONGLYZA as Add-On Combination Therapy with Insulin*
Efficacy Parameter | ONGLYZA 5 mg + Insulin (+/− Metformin) N=304 | Placebo + Insulin (+/− Metformin) N=151
Hemoglobin A1C (%) | N=300 | N=149
Baseline (mean) | 8.7 | 8.7
Change from baseline (adjusted mean†) | −0.7 | −0.3
Difference from placebo (adjusted mean†) | −0.4‡
95% Confidence Interval | (−0.6, −0.2)
Percent of patients achieving A1C <7% | 17% (52/300) | 7% (10/149)
Fasting Plasma Glucose (mg/dL) | N=300 | N=149
Baseline (mean) | 173 | 173
Change from baseline (adjusted mean†) | −10 | −6
Difference from placebo (adjusted mean†) | −4
95% Confidence Interval | (−13, 5)
2-hour Postprandial Glucose (mg/dL) | N=262 | N=129
Baseline (mean) | 251 | 255
Change from baseline (adjusted mean†) | −27 | −4
Difference from placebo (adjusted mean†) | −23§
95% Confidence Interval | (−37, −9)
* Intent-to-treat population using last observation on study or last observation prior to insulin rescue therapy for patients needing rescue.
† Least squares mean adjusted for baseline value and metformin use at baseline.
‡ p-value <0.0001 compared to placebo + insulin
§ p-value <0.05 compared to placebo + insulin

14.3 Renal Impairment

A total of 170 patients participated in a 12-week, randomized, double-blind, placebo-controlled trial conducted to evaluate the efficacy and safety of ONGLYZA 2.5 mg once daily compared with placebo in patients with type 2 diabetes and moderate (n=90) or severe (n=41) renal impairment or ESRD (n=39). In this trial, 98% of the patients were using background antidiabetic medications (75% were using insulin and 31% were using oral antidiabetic medications, mostly sulfonylureas).

After 12 weeks of treatment, ONGLYZA 2.5 mg provided significant improvement in A1C compared to placebo (Table 12). In the subgroup of patients with ESRD, ONGLYZA and placebo resulted in comparable reductions in A1C from baseline to Week 12. This finding is inconclusive because the trial was not adequately powered to show efficacy within specific subgroups of renal impairment.

After 12 weeks of treatment, the mean change in FPG was −12 mg/dL with ONGLYZA 2.5 mg and −13 mg/dL with placebo. Compared to placebo, the mean change in FPG with ONGLYZA was −12 mg/dL in the subgroup of patients with moderate renal impairment, −4 mg/dL in the subgroup of patients with severe renal impairment, and +44 mg/dL in the subgroup of patients with ESRD. These findings are inconclusive because the trial was not adequately powered to show efficacy within specific subgroups of renal impairment.

Table 12: A1C at Week 12 in a Placebo-Controlled Trial of ONGLYZA in Patients with Renal Impairment*
Efficacy Parameter | ONGLYZA 2.5 mg N=85 | Placebo N=85
Hemoglobin A1C (%) | N=81 | N=83
Baseline (mean) | 8.4 | 8.1
Change from baseline (adjusted mean†) | −0.9 | −0.4
Difference from placebo (adjusted mean†) | −0.4‡
95% Confidence Interval | (−0.7, −0.1)
* Intent-to-treat population using last observation on study.
† Least squares mean adjusted for baseline value.
‡ p-value <0.01 compared to placebo

16 HOW SUPPLIED/STORAGE AND HANDLING

HOW SUPPLIED

How Supplied

ONGLYZA® (saxagliptin) tablets have markings on both sides and are available in the strengths and packages listed in Table 12.

Table 12: ONGLYZA Tablet Presentations
Tablet Strength | Film-Coated Tablet Color/Shape | Tablet Markings | Package Size | NDC Code
5 mg | pink biconvex, round | “5” on one side and “4215” on the reverse, in blue ink | Bottles of 30 | 54868-6309-0

STORAGE AND HANDLING

Storage and Handling

Store at 20°-25°C (68°-77°F); excursions permitted to 15°-30°C (59°-86°F) [see USP Controlled Room Temperature].

17 PATIENT COUNSELING INFORMATION

See FDA-approved Medication Guide.

17.1 Instructions

Patients should be informed of the potential risks and benefits of ONGLYZA and of alternative modes of therapy. Patients should also be informed about the importance of adherence to dietary instructions, regular physical activity, periodic blood glucose monitoring and A1C testing, recognition and management of hypoglycemia and hyperglycemia, and assessment of diabetes complications. During periods of stress such as fever, trauma, infection, or surgery, medication requirements may change and patients should be advised to seek medical advice promptly.

Patients should be informed that acute pancreatitis has been reported during postmarketing use of ONGLYZA. Before initiating ONGLYZA, patients should be questioned about other risk factors for pancreatitis, such as a history of pancreatitis, alcoholism, gallstones, or hypertriglyceridemia. Patients should also be informed that persistent severe abdominal pain, sometimes radiating to the back, which may or may not be accompanied by vomiting, is the hallmark symptom of acute pancreatitis. Patients should be instructed to promptly discontinue ONGLYZA and contact their healthcare provider if persistent severe abdominal pain occurs [see Warnings and Precautions (5.1)].

Patients should be informed that serious allergic (hypersensitivity) reactions, such as angioedema, anaphylaxis, and exfoliative skin conditions, have been reported during postmarketing use of ONGLYZA. If symptoms of these allergic reactions (such as rash, skin flaking or peeling, urticaria, swelling of the skin, or swelling of the face, lips, tongue, and throat that may cause difficulty in breathing or swallowing) occur, patients must stop taking ONGLYZA and seek medical advice promptly.

Patients should be informed that if they miss a dose of ONGLYZA they should take the next dose as prescribed, unless otherwise instructed by their healthcare provider. Patients should be instructed not to take an extra dose the next day.

Healthcare providers should instruct their patients to read the Medication Guide before starting ONGLYZA therapy and to reread it each time the prescription is renewed. Patients should be instructed to inform their healthcare provider if they develop any unusual symptom or if any existing symptom persists or worsens.

Patients should be informed that ONGLYZA tablets must not be split or cut.

17.2 Laboratory Tests

Patients should be informed that response to all diabetic therapies should be monitored by periodic measurements of blood glucose and A1C, with a goal of decreasing these levels toward the normal range. A1C is especially useful for evaluating long-term glycemic control. Patients should be informed of the potential need to adjust their dose based on changes in renal function tests over time.

Manufactured by:
Bristol-Myers Squibb Company
Princeton, NJ 08543 USA

Marketed by:
Bristol-Myers Squibb Company
Princeton, NJ 08543
and
AstraZeneca Pharmaceuticals LP
Wilmington, DE 19850

1297954 / 1256314A3
Rev December 2011

Additional barcode labeling by:
Physicians Total Care, Inc.
Tulsa, Oklahoma 74146

MEDICATION GUIDE
ONGLYZA (on-GLY-zah)
(saxagliptin)
tablets

Read this Medication Guide carefully before you start taking ONGLYZA and each time you get a refill. There may be new information. This information does not take the place of talking with your healthcare provider about your medical condition or treatment. If you have any questions about ONGLYZA, ask your healthcare provider.

What is the most important information I should know about ONGLYZA?

Serious side effects can happen to people taking ONGLYZA, including inflammation of the pancreas (pancreatitis) which may be severe and lead to death.

Certain medical problems make you more likely to get pancreatitis.

Before you start taking ONGLYZA:

Tell your healthcare provider if you have ever had

- inflammation of your pancreas (pancreatitis)
- stones in your gallbladder (gallstones)
- a history of alcoholism
- high blood triglyceride levels

It is not known if having these medical problems will make you more likely to get pancreatitis with ONGLYZA.

Stop taking ONGLYZA and contact your healthcare provider right away if you have pain in your stomach area (abdomen) that is severe and will not go away. The pain may be felt going from your abdomen through to your back. The pain may happen with or without vomiting. These may be symptoms of pancreatitis.

What is ONGLYZA?

- ONGLYZA is a prescription medicine used with diet and exercise to control high blood sugar (hyperglycemia) in adults with type 2 diabetes.
- ONGLYZA lowers blood sugar by helping the body increase the level of insulin after meals.
- ONGLYZA is unlikely by itself to cause your blood sugar to be lowered to a dangerous level (hypoglycemia) because it does not work well when your blood sugar is low. However, hypoglycemia may still occur with ONGLYZA. Your risk for getting hypoglycemia is higher if you take ONGLYZA with some other diabetes medicines, such as a sulfonylurea or insulin.
- ONGLYZA is not for people with type 1 diabetes.
- ONGLYZA is not for people with diabetic ketoacidosis (increased ketones in your blood or urine).
- If you have had pancreatitis in the past, it is not known if you have a higher chance of getting pancreatitis while you take ONGLYZA.

It is not known if ONGLYZA is safe and effective in children younger than 18 years old.

Who should not take ONGLYZA?

Do not take ONGLYZA if you:

- are allergic to any ingredients in ONGLYZA. See the end of this Medication Guide for a complete list of ingredients in ONGLYZA.

Symptoms of a serious allergic reaction to ONGLYZA may include:
  - swelling of your face, lips, throat, and other areas on your skin
  - difficulty with swallowing or breathing
  - raised, red areas on your skin (hives)
  - skin rash, itching, flaking, or peeling

If you have these symptoms, stop taking ONGLYZA and contact your healthcare provider right away.

What should I tell my healthcare provider before taking ONGLYZA?

Before you take ONGLYZA, tell your healthcare provider if you:

- have kidney problems.
- are pregnant or plan to become pregnant. It is not known if ONGLYZA will harm your unborn baby. If you are pregnant, talk with your healthcare provider about the best way to control your blood sugar while you are pregnant.
- are breast-feeding or plan to breast-feed. ONGLYZA may be passed in your milk to your baby. Talk with your healthcare provider about the best way to feed your baby while you take ONGLYZA.

Tell your healthcare provider about all the medicines you take, including prescription and nonprescription medicines, vitamins, and herbal supplements.

Know the medicines you take. Keep a list of your medicines and show it to your healthcare provider and pharmacist when you get a new medicine.

ONGLYZA may affect the way other medicines work, and other medicines may affect how ONGLYZA works. Contact your healthcare provider if you will be starting or stopping certain other types of medications, such as antibiotics, or medicines that treat fungus or HIV/AIDS, because your dose of ONGLYZA might need to be changed.

How should I take ONGLYZA?

- Take ONGLYZA by mouth one time each day exactly as directed by your healthcare provider. Do not change your dose without talking to your healthcare provider.
- ONGLYZA can be taken with or without food.
- Do not split or cut ONGLYZA tablets.
- During periods of stress on the body, such as:
  - fever
  - trauma
  - infection
  - surgery

Contact your healthcare provider right away as your medication needs may change.

- Your healthcare provider should test your blood to measure how well your kidneys are working before and during your treatment with ONGLYZA. You may need a lower dose of ONGLYZA if your kidneys are not working well.
- Follow your healthcare provider’s instructions for treating blood sugar that is too low (hypoglycemia). Talk to your healthcare provider if low blood sugar is a problem for you.
- If you miss a dose of ONGLYZA, take it as soon as you remember. If it is almost time for your next dose, skip the missed dose. Just take the next dose at your regular time. Do not take two doses at the same time unless your healthcare provider tells you to do so. Talk to your healthcare provider if you have questions about a missed dose.
- If you take too much ONGLYZA, call your healthcare provider or Poison Control Center at 1-800-222-1222, or go to the nearest hospital emergency room right away.

What are the possible side effects of ONGLYZA?

ONGLYZA can cause serious side effects, including:

- See "What is the most important information I should know about ONGLYZA?"
- Allergic (hypersensitivity) reactions, such as:
  - swelling of your face, lips, throat, and other areas on your skin
  - difficulty with swallowing or breathing
  - raised, red areas on your skin (hives)
  - skin rash, itching, flaking, or peeling

If you have these symptoms, stop taking ONGLYZA and contact your healthcare provider right away.

Common side effects of ONGLYZA include:

- upper respiratory tract infection
- urinary tract infection
- headache

Low blood sugar (hypoglycemia) may become worse in people who also take another medication to treat diabetes, such as sulfonylureas or insulin. Tell your healthcare provider if you take other diabetes medicines. If you have symptoms of low blood sugar, you should check your blood sugar and treat if low, then call your healthcare provider. Symptoms of low blood sugar include:

- shaking
- sweating
- rapid heartbeat
- change in vision
- hunger
- headache
- change in mood

Swelling or fluid retention in your hands, feet, or ankles (peripheral edema) may become worse in people who also take a thiazolidinedione to treat diabetes. If you do not know whether you are already on this type of medication, ask your healthcare provider.

These are not all of the possible side effects of ONGLYZA. Tell your healthcare provider if you have any side effects that bother you or that do not go away. For more information, ask your healthcare provider.

Call your healthcare provider for medical advice about side effects. You may report side effects to the FDA at 1-800-FDA-1088.

How should I store ONGLYZA?

Store ONGLYZA between 68°F and 77°F (20°C and 25°C).

Keep ONGLYZA and all medicines out of the reach of children.

General information about the use of ONGLYZA

Medicines are sometimes prescribed for conditions that are not mentioned in Medication Guides. Do not use ONGLYZA for a condition for which it was not prescribed. Do not give ONGLYZA to other people, even if they have the same symptoms you have. It may harm them.

This Medication Guide summarizes the most important information about ONGLYZA. If you would like to know more information about ONGLYZA, talk with your healthcare provider. You can ask your healthcare provider for additional information about ONGLYZA that is written for healthcare professionals. For more information, go to www.ONGLYZA.com or call 1-800-ONGLYZA.

What are the ingredients of ONGLYZA?

Active ingredient: saxagliptin

Inactive ingredients: lactose monohydrate, microcrystalline cellulose, croscarmellose sodium, and magnesium stearate. In addition, the film coating contains the following inactive ingredients: polyvinyl alcohol, polyethylene glycol, titanium dioxide, talc, and iron oxides.

What is type 2 diabetes?

Type 2 diabetes is a condition in which your body does not make enough insulin, and the insulin that your body produces does not work as well as it should. Your body can also make too much sugar. When this happens, sugar (glucose) builds up in the blood. This can lead to serious medical problems.

The main goal of treating diabetes is to lower your blood sugar so that it is as close to normal as possible.

High blood sugar can be lowered by diet and exercise, and by certain medicines when necessary.

This Medication Guide has been approved by the U.S. Food and Drug Administration.

ONGLYZA (saxagliptin) tablets
Manufactured by:
Bristol-Myers Squibb Company
Princeton, NJ 08543 USA

Marketed by:
Bristol-Myers Squibb Company
Princeton, NJ 08543
and
AstraZeneca Pharmaceuticals LP
Wilmington, DE 19850

1297954 / 1256314A3 / 1296566A0
Rev December 2011

PACKAGE LABEL

---------------------------------------------
REPRESENTATIVE PACKAGING

See How Supplied section for a complete list of available packages of ONGLYZA.

30 Tablets
ONGLYZA®
(saxagliptin) tablets
5 mg
DISPENSE WITH MEDICATION GUIDE
Rx only